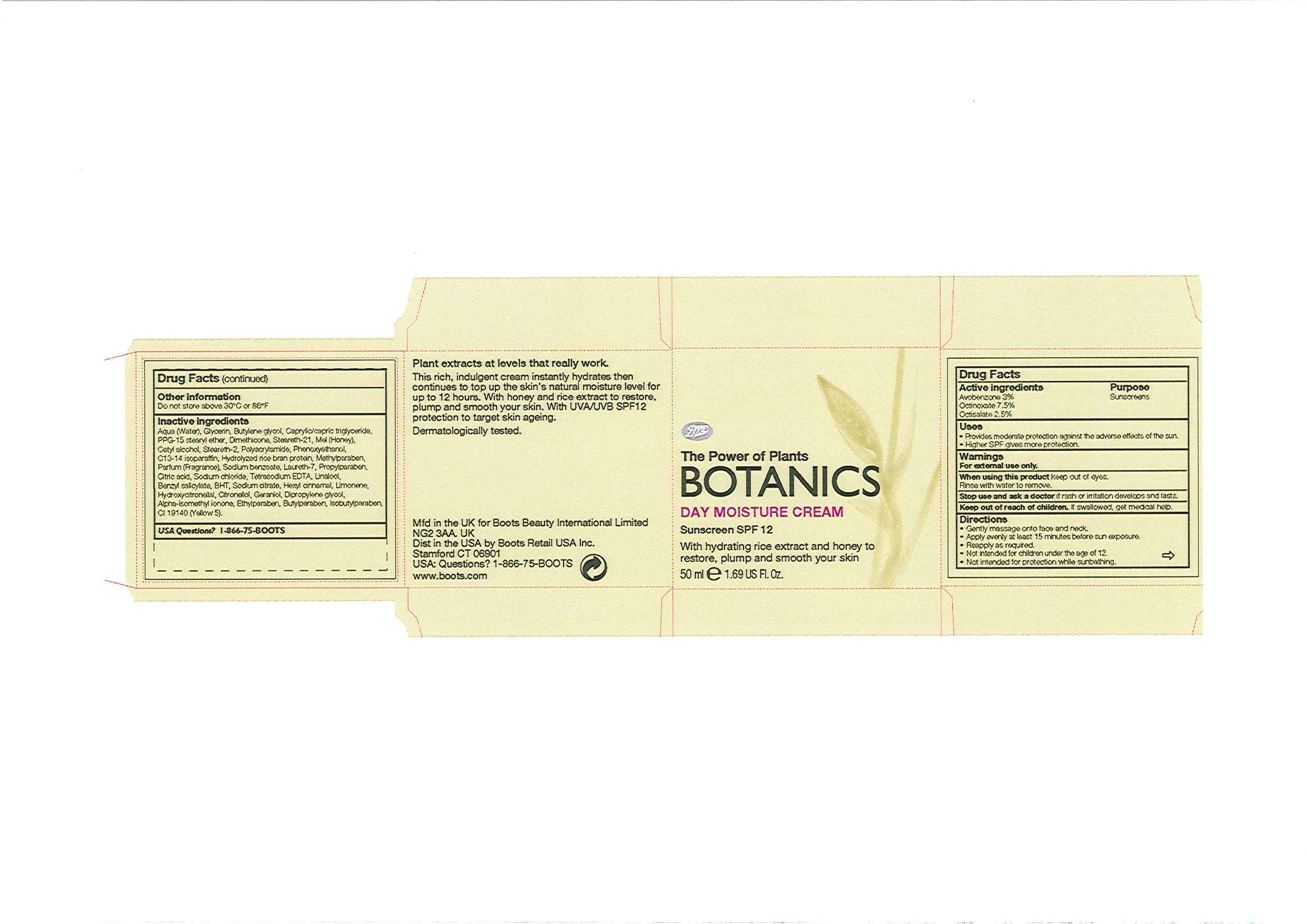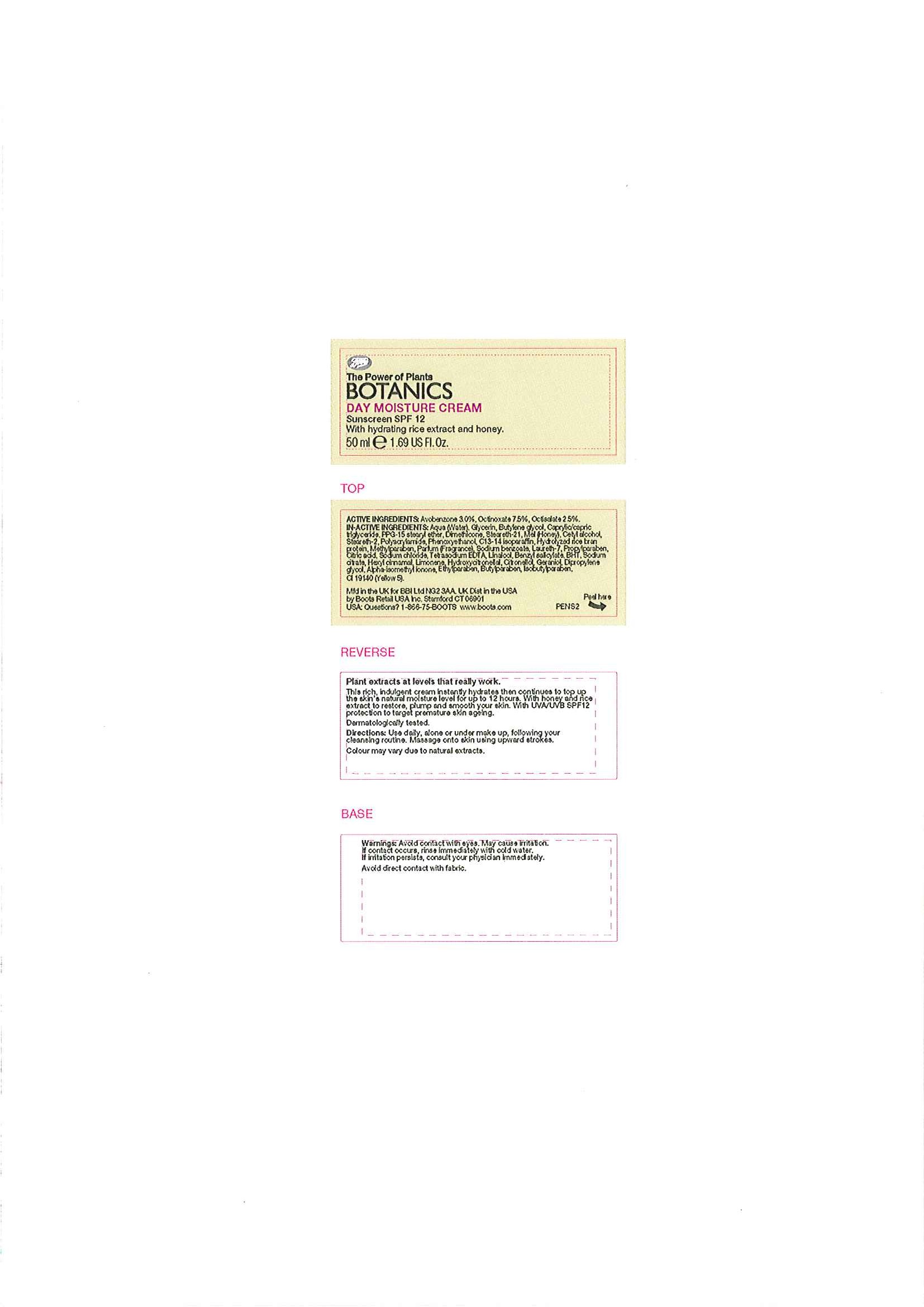 DRUG LABEL: Botanics Day Moisture Sunscreen SPF 12
NDC: 68472-074 | Form: CREAM
Manufacturer: Boots Retail USA Inc
Category: otc | Type: HUMAN OTC DRUG LABEL
Date: 20100803

ACTIVE INGREDIENTS: OCTINOXATE 3.75 mL/50 mL; AVOBENZONE 1.5 mL/50 mL; OCTISALATE 1.25 mL/50 mL
INACTIVE INGREDIENTS: WATER; GLYCERIN; BUTYLENE GLYCOL; MEDIUM-CHAIN TRIGLYCERIDES; DIMETHICONE; HONEY; CETYL ALCOHOL; PHENOXYETHANOL; C13-14 ISOPARAFFIN; RICE BRAN; METHYLPARABEN; SODIUM BENZOATE; PROPYLPARABEN; CITRIC ACID MONOHYDRATE; SODIUM CHLORIDE; EDETATE SODIUM; BUTYLATED HYDROXYTOLUENE; ETHYLPARABEN; BUTYLPARABEN; ISOBUTYLPARABEN; FD&C YELLOW NO. 5

carton and jar labelling

ACTIVE INGREDIENT

BOTANICS DAY MOISTURE CREAM SUNSCREEN SPF 12
Active Ingredients Purpose
Avobenzone 3% Sunscreens
Octinoxate 7.5%
Octisalate 2.5%

Uses

- Provides moderate protection against the adverse effects of the sun.
- Higher SPF gives more protection.

Warnings
For external use only.
When using this product keep out of eyes.
Rinse with water to remove.

Stop use and ask a doctor if rash or irritation develops and lasts.

Keep out of reach of children. If swallowed, get medical help.

Directions

- Gently massage onto face and neck.
- Apply evenly at least 15 minutes before sun exposure.
- Reapply as required.
- Not intended for children under the age of 12.
- Not intended for protection while sunbathing.

Other information

Do not store above 30oC or 86oF

Inactive ingredients

Aqua (Water), Glycerin, Butylene glycol, Caprylic/capric triglyceride, PPG-15 stearyl ether, Dimethicone, Steareth-21, Mel (Honey), Cetyl alcohol, Steareth-2, Polyacrylamide, Phenoxyethanol, C13-14 isoparaffin, Hydrolyzed rice bran protein, Methylparaben, Parfum (Fragrance), Sodium benzoate, Laureth-7, Propylparaben, Citric acid, Sodium chloride, Tetrasodium EDTA, Linalool, Benzyl salicylate, BHT, Sodium citrate, Hexyl cinnamal, Limonene, Hydroxycitronellal, Citronellol, Geraniol, Dipropylene glycol, Apha-isomethyl ionone, Ethylparaben, Butylparaben, Isobutylparaben, CI 19140 (Yellow 5).

USA Questions?1-866-75-BOOTS

DESCRIPTION

Plant extracts at levels that really work.

This rich, indulgent cream instantly hydrates then continues to top up the skin's natural moisture level for up to 12 hours. With honey and rice extract to restore, plump and smooth your skin. With UVA/UVB SPF12 protection to target skin ageing.

Dermatologically tested

PATIENT COUNSELING INFORMATION

Mfd in the UK for Boots Beauty International Limited

NG2 3AA. UK

Dist in the USA by Boots Retail USA Inc.

Stamford CT 06901

USA: Questions? 1-866-75-BOOTS

www.boots.com

ACTIVE INGREDIENT

ACTIVE INGREDIENTS: Avobenzone 3.0%, Octinoxate 7.5%, Octisalate 2.5%.

INACTIVE INGREDIENT

IN-ACTIVE INGREDIENTS: Aqua (Water), Glycerin, Butylene glycol, Caprylic/capric triglyceride, PPG-15 stearyl ether, Dimethicone, Steareth-21, Mel (Honey), Cetyl alcohol, Steareth-2, Polyacrylamide, Phenoxyethanol, C13-14 isoparaffin, Hydrolyzed rice bran protein, Methylparaben, Parfum (Fragrance), Sodium benzoate, Laureth-7, Propylparaben, Citric acid, Sodium chloride, Tetrasodium EDTA, Linalool, Benzyl salicylate, BHT, Sodium citrate, Hexyl cinnamal, Limonene, Hydroxycitronellal, Citronellol, Geraniol, Dipropylene glycol, Alpha-isomethyl ionone, Ethylparaben, Butylparaben, Isobutylparaben, CI 19140 (Yellow 5).

PATIENT COUNSELING INFORMATION

Mfd in the UK for BBI Ltd NG2 3AA. UK Dist in the USA

by Boots Retail USA Inc. Stamford CT 06901

USA: Questions? 1-866-75-BOOTS www.boots.com

DESCRIPTION

Plant extracts at levels that really work.

This rich, indulgent cream instantly hydrates then continues to top up the skin's natural moisture level for up to 12 hours. With honey and rice extract to restore, plump and smooth your skin. With UVA/UVB SPF12 protection to target premature skin ageing.

Dermatologically tested.

INDICATIONS AND USAGE

Directions: Use daily, alone or under make up, following your cleansing routine. Massage onto skin using upward strokes.

Colour may vary due to natural extracts.

Warnings: Avoid contact with eyes. May cause irritation.

If contact occurs, rinse immediately with cold water.

If irritation persists, consult your physician immediately.

Avoid direct contact with fabric.

PACKAGE LABEL

The Power of Plants

BOTANICS

DAY MOISTURE CREAM

Sunscreen SPF 12

With hydrating rice extract and honey to

restore, plump and smooth your skin.

50ml e 1.69 US Fl. Oz.

PACKAGE LABEL

The Power of Plants

BOTANICS

DAY MOISTURE CREAM

Sunscreen SPF 12

With hydrating rice extract and honey.

50ml e 1.69 US Fl. Oz.

HOW SUPPLIED

Colour may vary due to natural extracts.